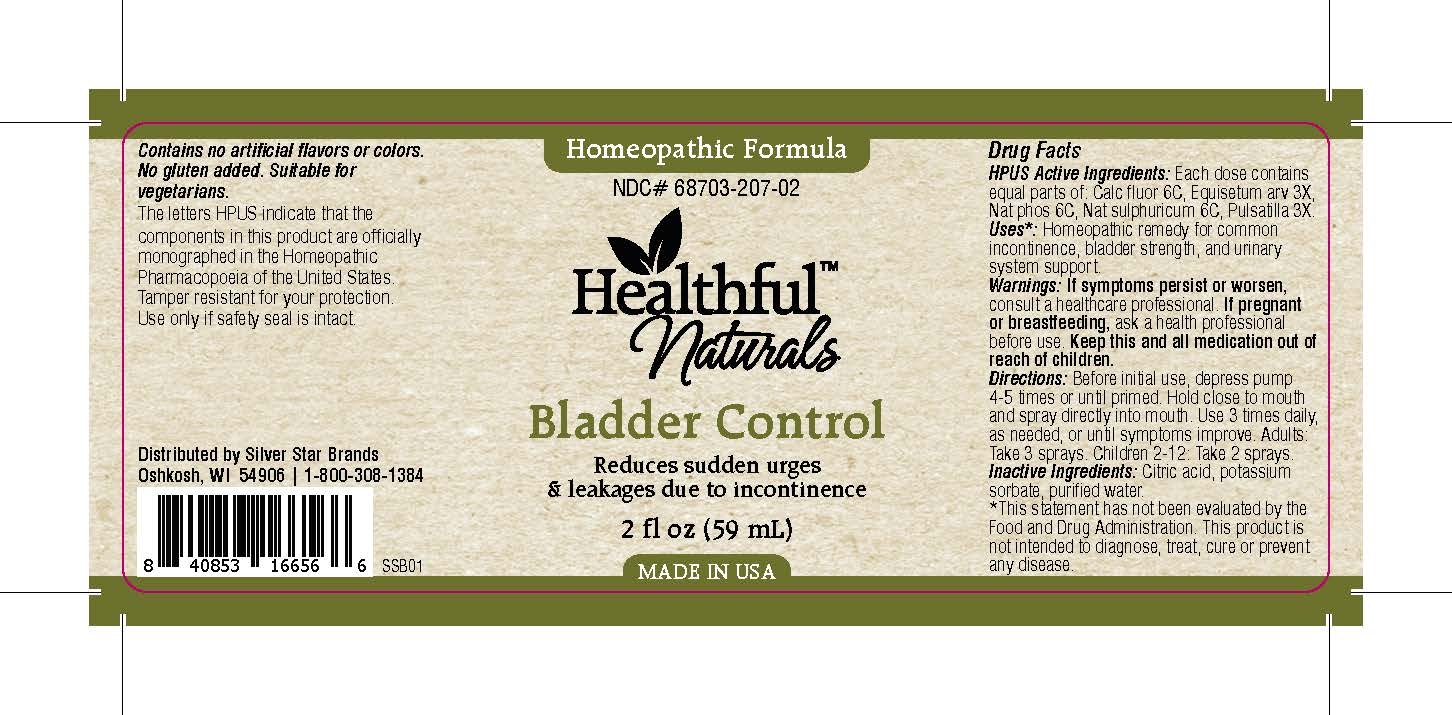 DRUG LABEL: Bladder Control
NDC: 68703-207 | Form: SPRAY
Manufacturer: Silver Star Brands
Category: homeopathic | Type: HUMAN OTC DRUG LABEL
Date: 20151110

ACTIVE INGREDIENTS: SODIUM PHOSPHATE, DIBASIC, HEPTAHYDRATE 6 [hp_C]/59 mL; EQUISETUM ARVENSE TOP 3 [hp_X]/59 mL; PULSATILLA VULGARIS 3 [hp_X]/59 mL; SODIUM SULFATE 6 [hp_C]/59 mL; CALCIUM FLUORIDE 6 [hp_C]/59 mL
INACTIVE INGREDIENTS: WATER; ANHYDROUS CITRIC ACID; POTASSIUM SORBATE

Healthful™ Naturals Bladder Control

HPUS Active Ingredients

Each dose contains equal parts of: Calc fluor 6C, Equisetum arv 3X, Nat phos 6C, Nat sulphuricum 6C, Pulsatilla 3X.

Uses

*Homeopathic remedy for common incontinence, bladder strength, and urinary system support. *This statement has not been evaluated by the Food and Drug Administration. This product is not intended to diagnose, treat, cure or prevent any disease.

Warnings

If symptoms persist or worsen, consult a healthcare professional. If pregnant or breastfeeding, ask a health professional before use. Keep this and all medication out of reach of children.

Directions

Before initial use, depress pump 4-5 times or until primed. Hold close to mouth and spray directly into mouth. Use 3 times daily, as needed, or until symptoms improve. Adults: Take 3 sprays. Children 2-12: Take 2 sprays.

OTHER SAFETY INFORMATION

Contains no artificial flavors or colors. No gluten added. Suitable for vegetarians. The letters HPUS indicate that the components in this product are officially monographed in the Homeopathic Pharmacopoeia of the United States. Tamper resistant for your protection. Use only if safety seal is intact.

INACTIVE INGREDIENT

Citric acid, potassium sorbate, purified water.

KEEP OUT OF REACH OF CHILDREN

Keep this and all medication out of reach of children.

PREGNANCY OR BREAST FEEDING

If pregnant or breastfeeding, ask a health professional before use.

PURPOSE

Reduces sudden urges & leakages due to incontinence